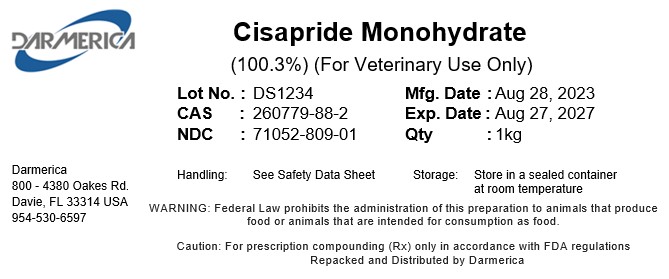 DRUG LABEL: Cisapride Monohydrate
NDC: 71052-809 | Form: POWDER
Manufacturer: DARMERICA, LLC
Category: other | Type: BULK INGREDIENT - ANIMAL DRUG
Date: 20251015

ACTIVE INGREDIENTS: CISAPRIDE MONOHYDRATE 1 kg/1 kg

Cisapride Monohydrate